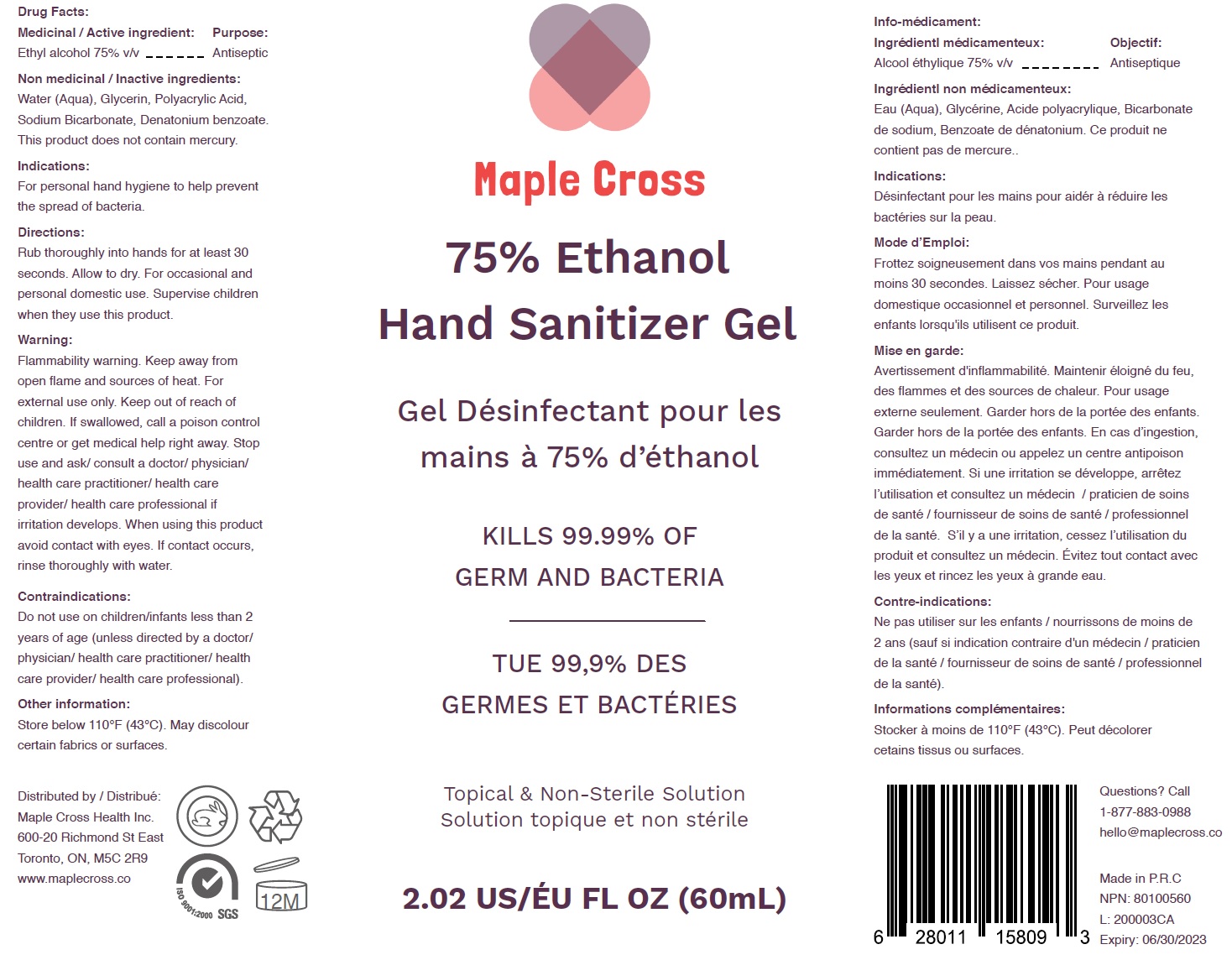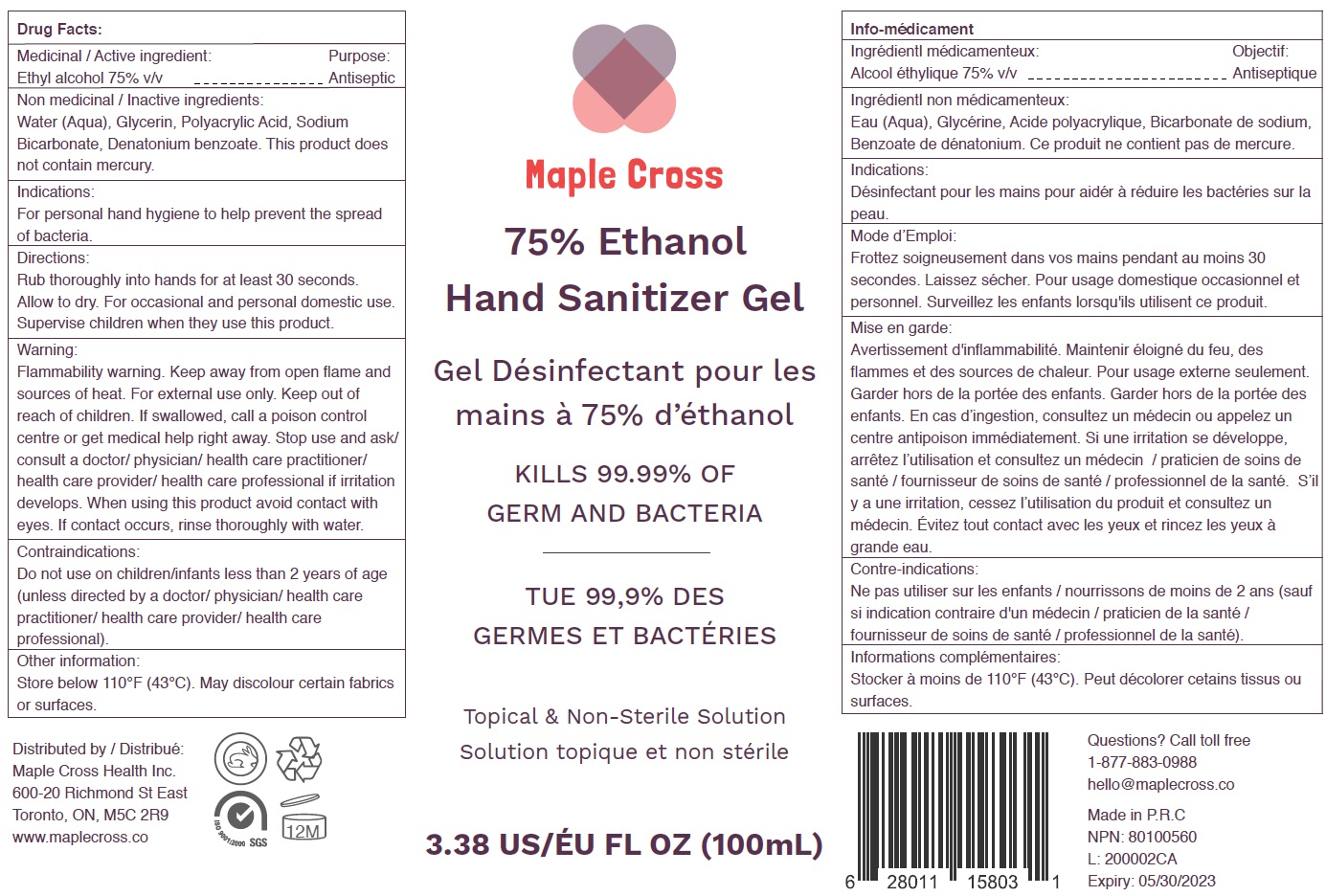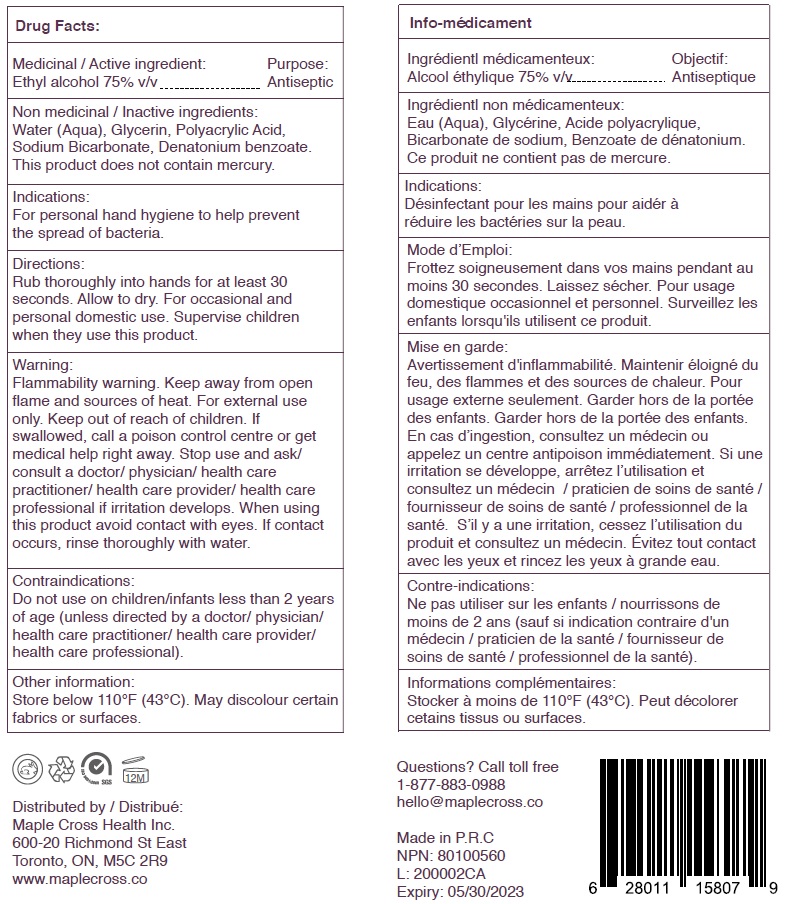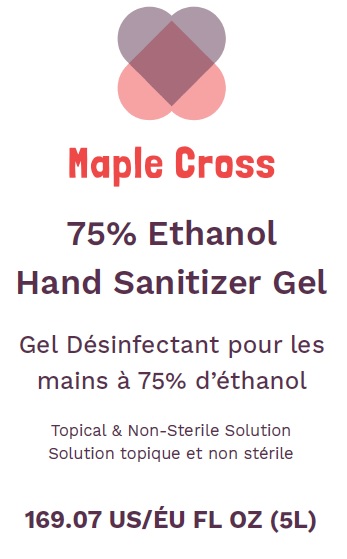 DRUG LABEL: Maple Cross Hand Sanitizer
NDC: 77216-002 | Form: GEL
Manufacturer: Maple Cross Health Inc.
Category: otc | Type: HUMAN OTC DRUG LABEL
Date: 20200623

ACTIVE INGREDIENTS: ALCOHOL 0.75 mL/1 mL
INACTIVE INGREDIENTS: WATER; GLYCERIN; SODIUM BICARBONATE; DENATONIUM BENZOATE

Maple Cross Hand Sanitizer Gel

Medicinal / Active ingredient:

Ethyl alcohol 75% v/v

Purpose:

Antiseptic

Non medicinal / Inactive ingredients:

Water (Aqua), Glycerin, Polyacrylic Acid, Sodium Bicarbonate, Denatonium benzoate. This product does not contain mercury.

Indications:

For personal hand hygiene to help prevent the spread of bacteria.

Directions:

Rub thoroughly into hands for at least 30 seconds. Allow to dry. For occasional and personal domestic use. Supervise children when they use this product.

Warning:

Flammability warning. Keep away from open flame and sources of heat. For external use only.

Keep out of reach of children.

If swallowed, call a poison control centre or get medical help right away.

Stop use and ask/ consult a doctor/

physician/ health care practitioner/ health care provider/ health care professional if irritation develops.

When using this product

avoid contact with eyes. If contact occurs, rinse thoroughly with water.

Contraindications:

Do not use on children/infants less than 2 years of age (unless directed by a doctor/ physician/ health care practitioner/ health care provider/ health care professional).

Other information:

Store below 110°F (43°C). May discolour certain fabrics or surfaces.